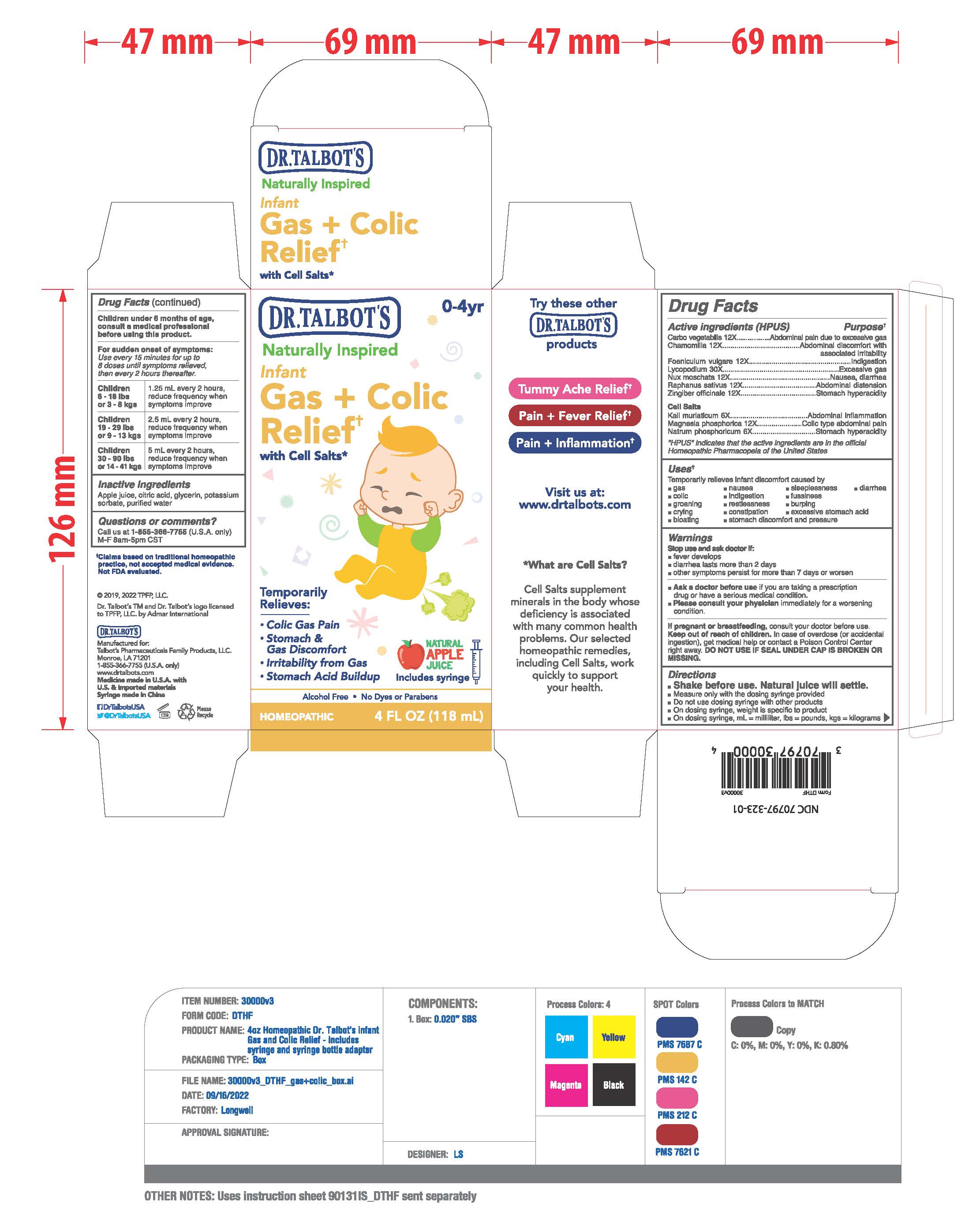 DRUG LABEL: Dr Talbots Infgant Gas Colic Relief
NDC: 70797-323 | Form: LIQUID
Manufacturer: Talbot's Pharmaceuticals Family Products,LLC.
Category: homeopathic | Type: HUMAN OTC DRUG LABEL
Date: 20220928

ACTIVE INGREDIENTS: SODIUM PHOSPHATE, DIBASIC, HEPTAHYDRATE 6 [hp_X]/118 mL; RADISH 12 [hp_X]/118 mL; MAGNESIUM PHOSPHATE, DIBASIC TRIHYDRATE 12 [hp_X]/118 mL; LYCOPODIUM CLAVATUM SPORE 30 [hp_X]/118 mL; GINGER 12 [hp_X]/118 mL; MATRICARIA CHAMOMILLA 12 [hp_X]/118 mL; NUTMEG 12 [hp_X]/118 mL; FENNEL SEED 12 [hp_X]/118 mL; POTASSIUM CHLORIDE 6 [hp_X]/118 mL; ACTIVATED CHARCOAL 12 [hp_X]/118 mL
INACTIVE INGREDIENTS: APPLE JUICE; CITRIC ACID MONOHYDRATE; GLYCERIN; WATER; POTASSIUM SORBATE

ACTIVE INGREDIENTS

Active ingredients (HPUS)

Carbo vegetabilis 12X

Chamomilla 12X

Foeniculum vulgare 12X

Lycopodium 30X

Nux moschata 12X

Raphanus sativus 12X

Zingiber officinale 12X

Cell Salts

Kali muriaticum 6X

Magnesia phosphorica 12X

Natrum phosphoricum 6X

INACTIVE INGREDIENTS

Apple juice, citric acid, glycerin, potassium
sorbate, purified water

PREGNANCY

If pregnant or breastfeeding, consult your doctor before use.

Ask a doctor before use if you are taking a prescription drugs or have a serious medical condition.

Please consult your physician immiediately for a worsening condition.

QUESTIONS

Questions or comments?
Call us at 1-855-366-7755 (U.S.A. only)
M-F 8am-5pm CST

Keep out of reach of children. In case of overdose (or accidental ingestion), get medical help or contact a Poison Control Center right away. DO NOT USE IF SEAL UNDER CAP IS BROKEN OR MISSING.

DOSAGE

Children under 6 months of age, consult a medical professional before using this product.
For sudden onset of symptoms: Use every 15 minutes for up to 8 doses until symptoms relieved, every 2 hours thereafter.

Uses

Uses: Temporarily relieves infant discomfort caused by

- gas
- nausea
- fussiness
- colic
- indigestion
- burping
- groaning
- restlesness
- sleeplessness
- diarrhea
- crying
- constipation
- ecxessive stomach acid
- bloating
- stomach discomfort and presure

PURPOSE

Temprorily Relieves:

- Colic Gas Pain
- Stomach & Gas Discomfort
- Irritability from Gas
- Stomach Acid Buildup

WARNINGS

Stop use and ask doctor if:

- fever develops.
- diarrhea lasts more than 2 days.
- other symptoms persist for more than 7 days or worsen.

PRINCIPAL DISPLAY PANEL

Label Display: